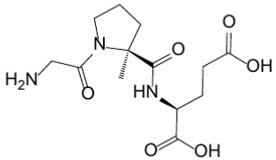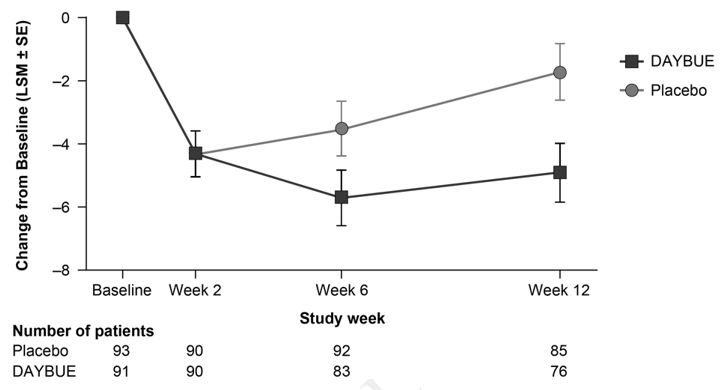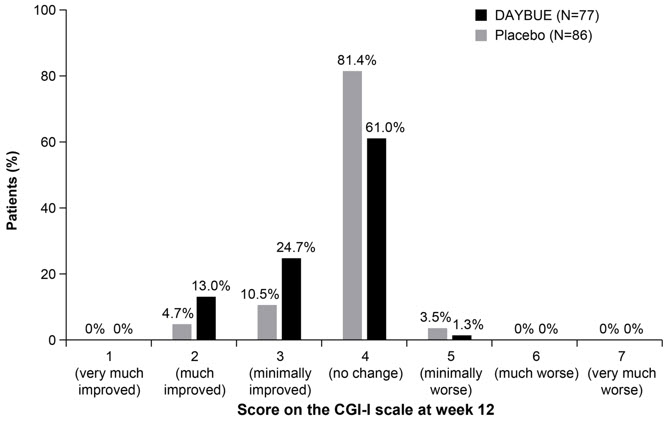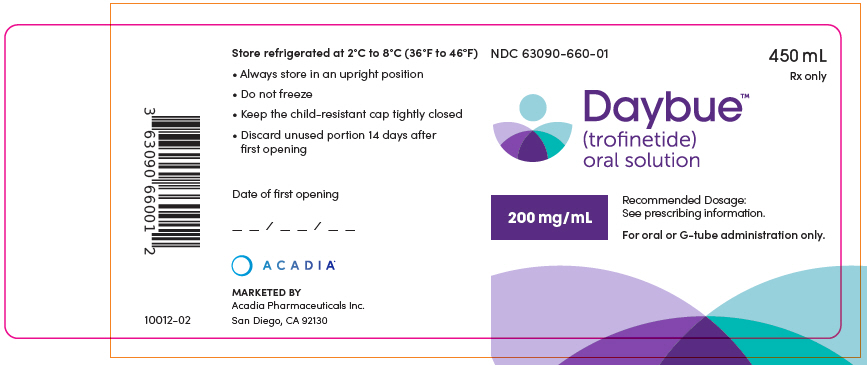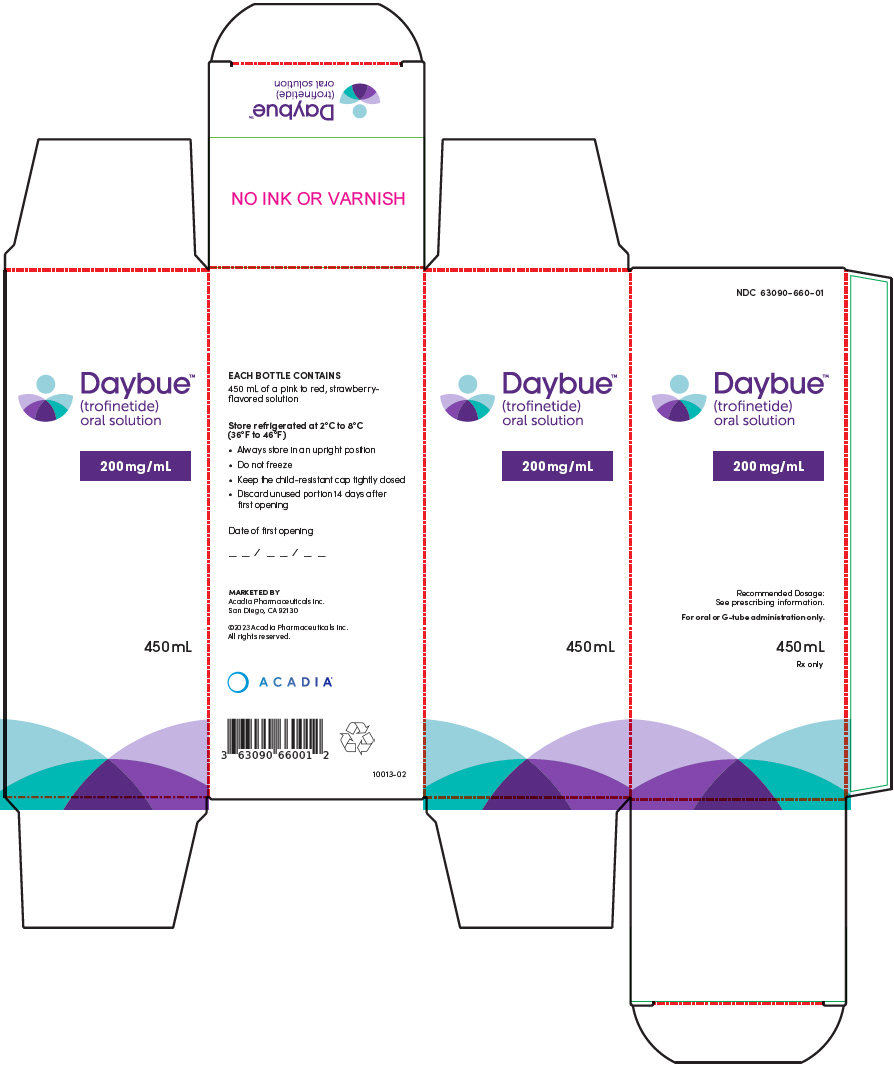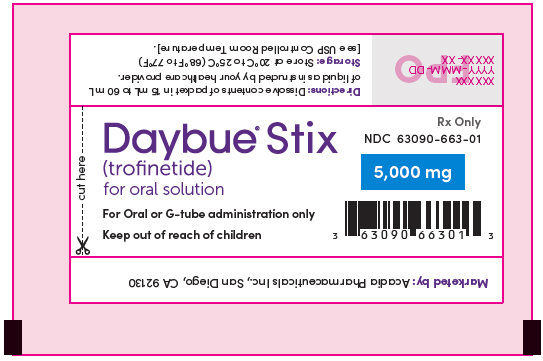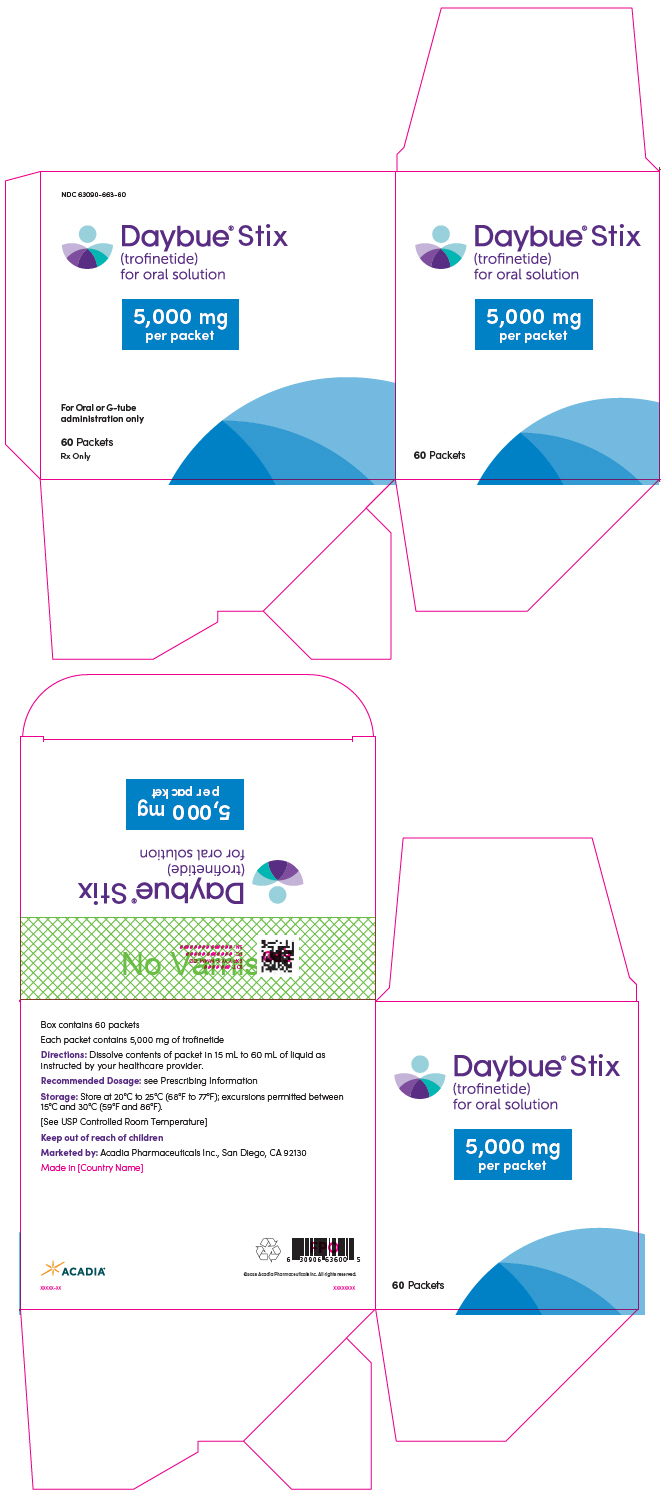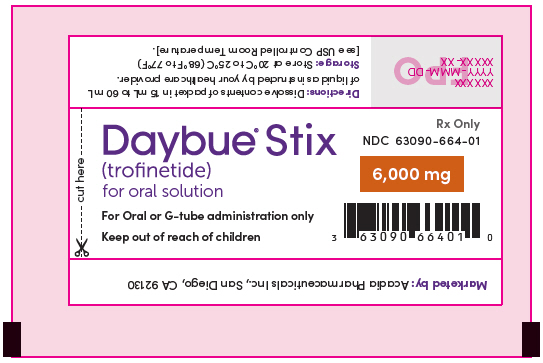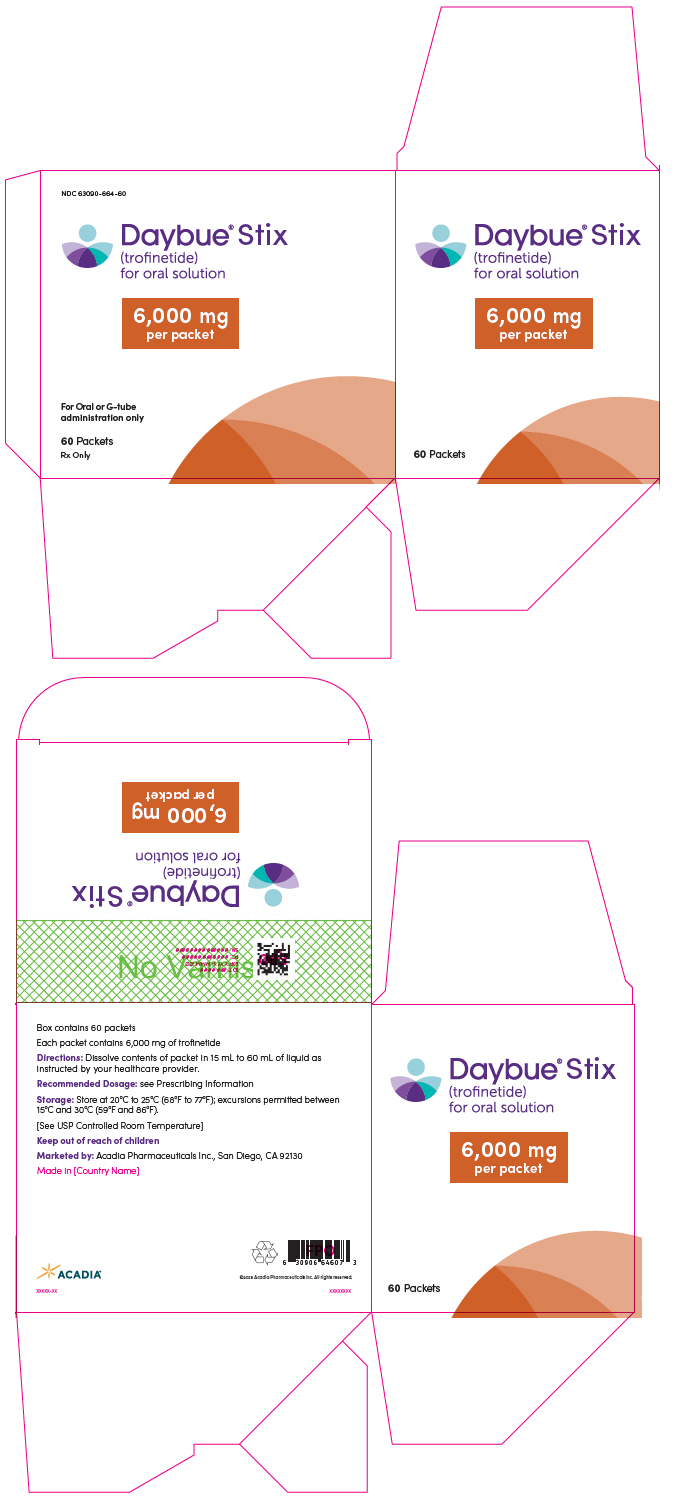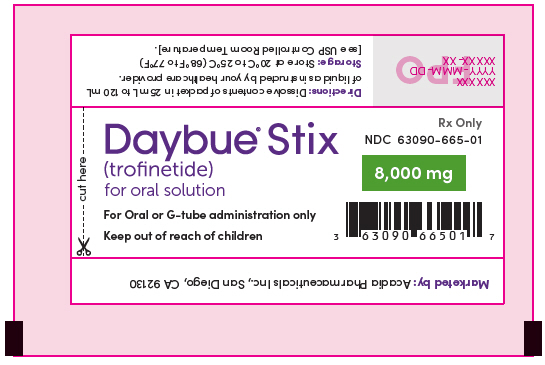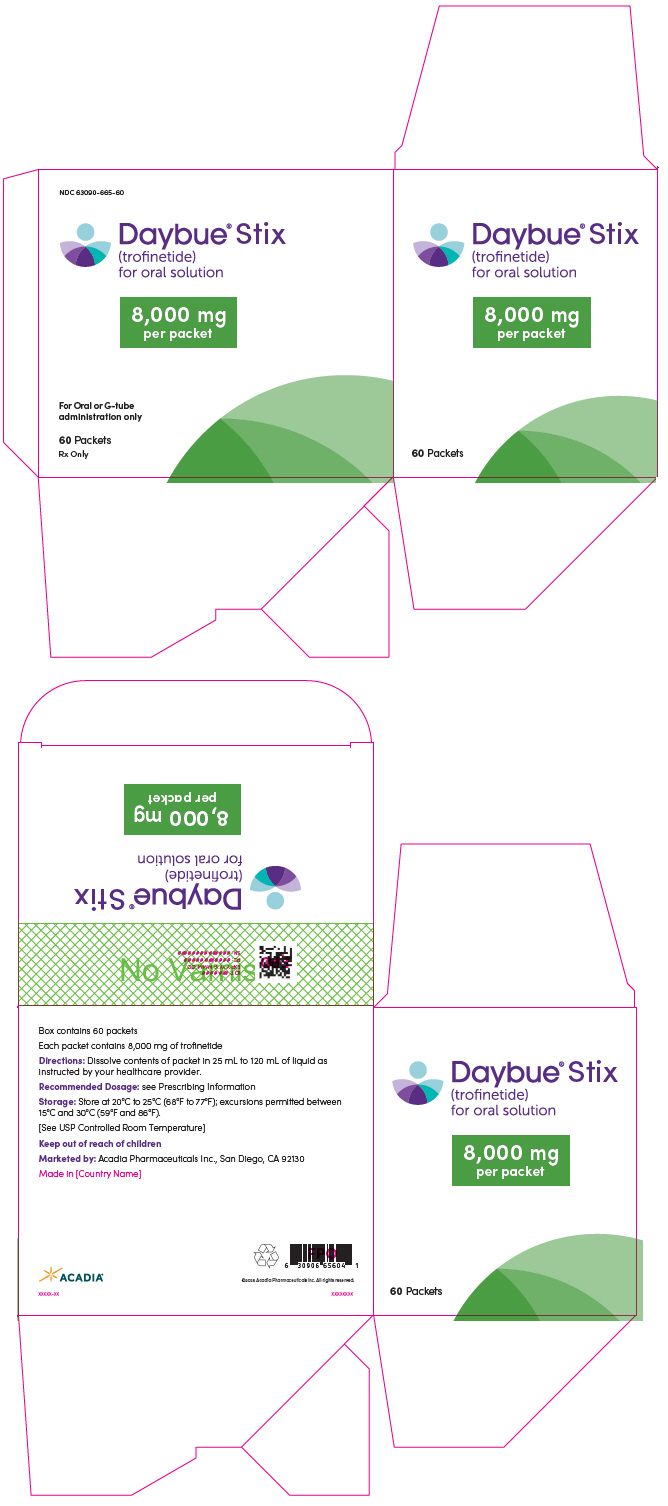 DRUG LABEL: Daybue
NDC: 63090-660 | Form: SOLUTION
Manufacturer: Acadia Pharmaceuticals Inc.
Category: prescription | Type: HUMAN PRESCRIPTION DRUG LABEL
Date: 20251217

ACTIVE INGREDIENTS: trofinetide 200 mg/1 mL
INACTIVE INGREDIENTS: maltitol; methylparaben sodium; propylparaben sodium; FD&C RED NO. 40; sucralose; water

HIGHLIGHTS OF PRESCRIBING INFORMATION

These highlights do not include all the information needed to use DAYBUE or DAYBUE STIX safely and effectively. See full prescribing information for DAYBUE and DAYBUE STIX.
DAYBUE® (trofinetide) oral solution
DAYBUE® STIX (trofinetide) for oral solution
Initial U.S. Approval: 2023

RECENT MAJOR CHANGES

Dosage and Administration (2.1, 2.2, 2.3, 2.6) | 12/2025

1 INDICATIONS AND USAGE

DAYBUE and DAYBUE STIX are indicated for the treatment of Rett syndrome in adults and pediatric patients 2 years of age and older. (1)

2 DOSAGE AND ADMINISTRATION

- Recommended dosage is twice daily, morning and evening, according to patient weight. DAYBUE or DAYBUE STIX can be given with or without food. (2.1)

Patient Weight | Recommended Dosage
9 kg to less than 12 kg | 5,000 mg twice daily
12 kg to less than 20 kg | 6,000 mg twice daily
20 kg to less than 35 kg | 8,000 mg twice daily
35 kg to less than 50 kg | 10,000 mg twice daily
50 kg or more | 12,000 mg twice daily

- Can be given orally or via gastrostomy (G) tube; doses administered via gastrojejunal (GJ) tubes must be administered through the G-port. (2.1)
- See Full Prescribing Information for instruction on dissolving DAYBUE STIX for oral solution powder. (2.3)
- See Full Prescribing Information for dosage recommendations in patients with renal impairment. (2.6, 8.6)

3 DOSAGE FORMS AND STRENGTHS

- Oral solution: 200 mg/mL (3)
- For oral solution: 5,000 mg, 6,000 mg, or 8,000 mg per packet (3)

4 CONTRAINDICATIONS

None. (4)

5 WARNINGS AND PRECAUTIONS

- Diarrhea: Most patients experience diarrhea during treatment with DAYBUE. Advise patients to stop laxatives before starting DAYBUE or DAYBUE STIX. If diarrhea occurs, patients should start antidiarrheal treatment, increase oral fluids, and notify their healthcare provider. Interrupt, reduce dose, or discontinue DAYBUE or DAYBUE STIX if severe diarrhea occurs or if dehydration is suspected. (2.4, 5.1)
- Weight Loss: Weight loss may occur in patients treated with DAYBUE or DAYBUE STIX. Monitor weight and interrupt, reduce dose, or discontinue DAYBUE or DAYBUE STIX if significant weight loss occurs. (2.4, 5.2)
- Vomiting: Aspiration and aspiration pneumonia have occurred after vomiting in patients treated with DAYBUE. Interrupt, reduce dose, or discontinue DAYBUE or DAYBUE STIX if vomiting is severe or occurs despite medical management. (2.5, 5.3)

6 ADVERSE REACTIONS

The most common adverse reactions (that occurred in at least 10% of DAYBUE-treated patients and at least 2% greater than in placebo) were diarrhea and vomiting. (6.1)

To report SUSPECTED ADVERSE REACTIONS, contact Acadia Pharmaceuticals Inc. at 1-844-422-2342 or FDA at 1-800-FDA-1088 or www.fda.gov/medwatch.

7 DRUG INTERACTIONS

- Orally administered CYP3A and/or P-gp sensitive substrates for which a small change in substrate plasma concentration may lead to serious adverse reactions: closely monitor for adverse reactions with concomitant use. (7.1)

8 USE IN SPECIFIC POPULATIONS

Severe renal impairment: DAYBUE and DAYBUE STIX are not recommended. (8.6)

FULL PRESCRIBING INFORMATION

1 INDICATIONS AND USAGE

DAYBUE and DAYBUE STIX are indicated for the treatment of Rett syndrome in adults and pediatric patients 2 years of age and older.

2 DOSAGE AND ADMINISTRATION

2.1 Recommended Dosage

The recommended dosage of DAYBUE or DAYBUE STIX is based on patient weight as shown in Table 1. Administer DAYBUE or DAYBUE STIX orally or via gastrostomy (G) tube twice daily, in the morning and evening, with or without food. Doses administered via gastrojejunal (GJ) tubes must be administered through the G-port.

Table 1 Recommended Dosage of DAYBUE or DAYBUE STIX in Patients 2 Years of Age and Older
Patient Weight | Recommended Dosage
9 kg to less than 12 kg | 5,000 mg twice daily
12 kg to less than 20 kg | 6,000 mg twice daily
20 kg to less than 35 kg | 8,000 mg twice daily
35 kg to less than 50 kg | 10,000 mg twice daily
50 kg or more | 12,000 mg twice daily

2.2 DAYBUE Oral Solution Preparation

Table 2 includes the volume of DAYBUE oral solution to administer for the corresponding recommended dosage [see Dosage and Administration (2.1, 2.6)]. A calibrated measuring device, such as an oral syringe or oral dosing cup, should be obtained from the pharmacy to measure and deliver the prescribed dose accurately. A household measuring cup, teaspoon, or tablespoon is not an adequate measuring device.

Table 2 Recommended Volume of DAYBUE Oral Solution for Administration
Dosage | DAYBUE Oral Solution Volume
2,500 mg twice daily [Dosage for patients with moderate renal impairment [see Dosage and Administration (2.6)]] | 12.5 mL twice daily
3,000 mg twice daily | 15 mL twice daily
4,000 mg twice daily | 20 mL twice daily
5,000 mg twice daily | 25 mL twice daily
6,000 mg twice daily | 30 mL twice daily
8,000 mg twice daily | 40 mL twice daily
10,000 mg twice daily | 50 mL twice daily
12,000 mg twice daily | 60 mL twice daily

Discard any unused DAYBUE oral solution after 14 days of first opening the bottle [see How Supplied/Storage and Handling (16.2)].

2.3 DAYBUE STIX for Oral Solution Preparation

Prior to administration, DAYBUE STIX for oral solution powder must be dissolved in a cold to room temperature water or water-based beverage (juice, tea, lemonade, limeade, or liquid hydration).

Preparation of DAYBUE STIX

1. Determine the correct dosage as shown in Table 1 or Table 4 (for patients with moderate renal impairment).
2. Select the appropriate packet strength and number of packets required for each dose, as shown in Table 3.
3. Determine the appropriate volume of liquid within the recommended volume range as shown in Table 3, based on individual patient factors (e.g., age, palatability).
4. Measure the volume of liquid determined in Step 3 by using a calibrated measuring device obtained from the pharmacy.
5. Empty the entire contents of the DAYBUE STIX packet(s) into the measured liquid. Do not attempt to use partial packets to prepare a dose.
6. Stir until the powder is completely dissolved.
7. Administer the prepared oral solution immediately; do not store for future use.
8. Discard any prepared oral solution that is not immediately administered.

Table 3 Preparation Instructions for DAYBUE STIX for Oral Solution Powder
Dose | DAYBUE STIX Packet(s) Needed to Prepare Each Dose | Volume of Liquid Required to Dissolve Entire Dose [Liquid types include water or water-based beverage.] , [Volume should be selected within the recommended range based on individual patient factors.]
5,000 mg | One 5,000 mg packet | 15 mL to 60 mL
6,000 mg | One 6,000 mg packet | 15 mL to 60 mL
8,000 mg | One 8,000 mg packet | 25 mL to 120 mL
10,000 mg | Two 5,000 mg packets | 30 mL to 120 mL (each packet requires 15 mL to 60 mL)
12,000 mg | Two 6,000 mg packets | 30 mL to 120 mL (each packet requires 15 mL to 60 mL)

2.4 Dose Modification for Diarrhea or Weight Loss

Advise patients to stop laxatives before starting DAYBUE or DAYBUE STIX. Interrupt, reduce dose, or discontinue DAYBUE or DAYBUE STIX if severe diarrhea occurs, if dehydration is suspected, or if significant weight loss occurs [see Warnings and Precautions (5.1, 5.2)].

2.5 Dose Modification for Vomiting After Administration

If vomiting occurs after DAYBUE or DAYBUE STIX administration, an additional dose should not be taken. Instead, continue with the next scheduled dose. Interrupt, reduce dose, or discontinue DAYBUE or DAYBUE STIX if vomiting is severe or occurs despite medical management [see Warnings and Precautions (5.3)].

2.6 Dosage Recommendations in Patients with Renal Impairment

No dosage adjustment is recommended for patients with mild renal impairment (estimated glomerular filtration rate [eGFR] 60 to 89 mL/min for adult patients or 60 to 89 mL/min/1.73 m^2 for pediatric patients). The recommended dosage of DAYBUE or DAYBUE STIX for patients with moderate renal impairment (eGFR 30 to 59 mL/min for adult patients or 30 to 59 mL/min/1.73 m^2 for pediatric patients) is described in Table 4 [see Use in Specific Populations (8.6), Clinical Pharmacology (12.3)]. DAYBUE and DAYBUE STIX are not recommended for patients with severe renal impairment (eGFR less than 30 mL/min for adult patients or less than 30 mL/min/1.73 m^2 for pediatric patients).

For patients with moderate renal impairment who require a dose less than 5,000 mg, DAYBUE oral solution is recommended. Do not attempt to use partial packets of DAYBUE STIX to prepare a dose.

Table 4 Recommended Dosage of DAYBUE or DAYBUE STIX in Patients with Moderate Renal Impairment
Patient Weight | Recommended Dosage
9 kg to less than 12 kg | 2,500 mg twice daily [Use DAYBUE oral solution to administer this dosage.]
12 kg to less than 20 kg | 3,000 mg twice daily
20 kg to less than 35 kg | 4,000 mg twice daily
35 kg to less than 50 kg | 5,000 mg twice daily
50 kg or more | 6,000 mg twice daily

2.7 Missed Dose

If a dose of DAYBUE or DAYBUE STIX is missed, the next dose should be taken as scheduled. Doses should not be doubled.

3 DOSAGE FORMS AND STRENGTHS

Oral solution: 200 mg/mL of a pink to red, strawberry flavored solution.

For oral solution: 5,000 mg, 6,000 mg, or 8,000 mg of white, off-white to pinkish powder with strawberry flavor, packaged in individual packets.

4 CONTRAINDICATIONS

None.

5 WARNINGS AND PRECAUTIONS

5.1 Diarrhea

In Study 1 [see Clinical Studies (14)] and in long-term studies, 85% of patients treated with DAYBUE experienced diarrhea. In those treated with DAYBUE, 49% either had persistent diarrhea or recurrence after resolution despite dose interruptions, reductions, or concomitant antidiarrheal therapy. Diarrhea severity was of mild or moderate severity in 96% of cases. In Study 1, antidiarrheal medication was used in 51% of patients treated with DAYBUE.

Advise patients to stop laxatives before starting DAYBUE or DAYBUE STIX. If diarrhea occurs, patients should notify their healthcare provider, consider starting antidiarrheal treatment, and monitor hydration status and increase oral fluids, if needed. Interrupt, reduce dose, or discontinue DAYBUE or DAYBUE STIX if severe diarrhea occurs or if dehydration is suspected [see Dosage and Administration (2.4)].

5.2 Weight Loss

In Study 1, 12% of patients treated with DAYBUE experienced weight loss of greater than 7% from baseline, compared to 4% of patients who received placebo. In long-term studies, 2.2% of patients discontinued treatment with DAYBUE due to weight loss.

Monitor weight and interrupt, reduce dose, or discontinue DAYBUE or DAYBUE STIX if significant weight loss occurs [see Dosage and Administration (2.4)].

5.3 Vomiting

In Study 1, vomiting occurred in 29% of patients treated with DAYBUE and in 12% of patients who received placebo [see Adverse Reactions (6.1)].

Patients with Rett syndrome are at risk for aspiration and aspiration pneumonia. Aspiration and aspiration pneumonia have been reported following vomiting in patients being treated with DAYBUE. Interrupt, reduce dose, or discontinue DAYBUE or DAYBUE STIX if vomiting is severe or occurs despite medical management [see Dosage and Administration (2.5)].

6 ADVERSE REACTIONS

The following clinically significant adverse reactions are described elsewhere in labeling:

- Diarrhea [see Warnings and Precautions (5.1)]
- Weight Loss [see Warnings and Precautions (5.2)]
- Vomiting [see Warnings and Precautions (5.3)]

6.1 Clinical Trials Experience

Because clinical trials are conducted under widely varying conditions, adverse reaction rates observed in the clinical trials of a drug cannot be directly compared to rates in the clinical trials of another drug and may not reflect the rates observed in practice.

In controlled and uncontrolled trials in patients with Rett syndrome, 260 patients ages 2 to 40 years were treated with DAYBUE, including 109 patients treated for more than 6 months, 69 patients treated for more than 1 year, and 4 patients treated for more than 2 years.

The safety of DAYBUE STIX has been established from an adequate, well-controlled study, and open-label studies of DAYBUE [see Clinical Studies (14)]. Below is a display of the adverse reactions of DAYBUE in these studies.

Adult and Pediatric Patients with Rett Syndrome 5 Years of Age and Older

The safety of DAYBUE was evaluated in a randomized, double-blind, placebo-controlled, 12-week study of patients with Rett syndrome (Study 1) [see Clinical Studies (14)]. In Study 1, 93 patients received DAYBUE and 94 patients received placebo. All patients were female, 92% were White, and the mean age was 11 years (range 5 to 20 years).

Adverse Reactions Leading to Discontinuation of Treatment

Eighteen patients (19%) receiving DAYBUE had adverse reactions that led to withdrawal from the study. The most common adverse reaction leading to discontinuation of treatment with DAYBUE was diarrhea (15%).

Common Adverse Reactions

Adverse reactions that occurred in Study 1 in at least 5% of patients treated with DAYBUE and were at least 2% more frequent than in patients on placebo are presented in Table 5.

Table 5 Adverse Reactions in at Least 5% of Patients Treated with DAYBUE and at Least 2% Greater than Placebo in Study 1
Adverse Reaction | DAYBUE (N=93) % | Placebo (N=94) %
Diarrhea | 82 | 20
Vomiting | 29 | 12
Fever | 9 | 4
Seizure | 9 | 6
Anxiety | 8 | 1
Decreased appetite | 8 | 2
Fatigue | 8 | 2
Nasopharyngitis | 5 | 1

Pediatric Patients with Rett Syndrome 2 to 4 Years of Age

In an open-label study in pediatric patients 2 to 4 years of age with Rett syndrome, a total of 13 patients received DAYBUE for at least 12 weeks and 9 patients received DAYBUE for at least 6 months. Adverse reactions in pediatric patients 2 to 4 years of age treated with DAYBUE were similar to those reported in adult and pediatric patients 5 years of age and older with Rett syndrome in Study 1.

6.2 Postmarketing Experience

The following adverse reactions have been identified during postapproval use of DAYBUE. Because these reactions are reported voluntarily from a population of uncertain size, it is not always possible to reliably estimate their frequency or establish a causal relationship to drug exposure.

Aspiration and aspiration pneumonia secondary to vomiting [see Warnings and Precautions (5.3)].

7 DRUG INTERACTIONS

7.1 Effect of DAYBUE and DAYBUE STIX on Other Drugs

CYP3A and/or P-gp Substrates

Closely monitor patients when DAYBUE or DAYBUE STIX is administered concomitantly with sensitive CYP3A and/or P-gp substrates where minimal increases in the plasma concentration of these substrates may lead to serious adverse reactions. Trofinetide, a weak inhibitor of CYP3A and an inhibitor of P-gp, increased the plasma concentrations of CYP3A and/or P-gp substrates [see Clinical Pharmacology (12.3)], which may increase the risk of adverse reactions associated with these substrates.

8 USE IN SPECIFIC POPULATIONS

8.1 Pregnancy

Risk Summary

There are no adequate data on the developmental risks associated with the use of DAYBUE or DAYBUE STIX in pregnant women. No adverse developmental effects were observed following oral administration of trofinetide to pregnant animals at doses associated with plasma exposures below those used clinically [see Animal Data].

The estimated background risk of major birth defects and miscarriage for the indicated population is unknown. In the U.S. general population, the estimated background risk of major birth defects and miscarriage in clinically recognized pregnancies is 2 to 4% and 15 to 20%, respectively.

Data

Animal Data

Oral administration of trofinetide (0, 150, 450, or 1000 mg/kg twice daily; 0, 300, 900, or 2000 mg/kg/day) to pregnant rats during the period of organogenesis resulted in no adverse effects on embryofetal development. At the highest dose tested, plasma exposure (AUC) was less than that in humans at the maximum recommended human dose (MRHD) of 12,000 mg twice daily (24,000 mg/day).

Oral administration of trofinetide (0, 75, 150, or 300 mg/kg twice daily; 0, 150, 300, or 600 mg/kg/day) to pregnant rabbits during the period of organogenesis resulted in no adverse effects on embryofetal development. At the highest dose tested, plasma exposure (AUC) was less than that in humans at the MRHD.

Oral administration of trofinetide (0, 150, 450, or 1000 mg/kg twice daily; 0, 300, 900, or 2000 mg/kg/day) to rats throughout pregnancy and lactation resulted in no adverse effects on pre- and postnatal development. At the highest dose tested, plasma exposure (AUC) was less than that in humans at the MRHD.

8.2 Lactation

Risk Summary

There is no information regarding the presence of trofinetide or its metabolites in human milk, the effects on the breastfed infant, or the effects on milk production. The developmental and health benefits of breastfeeding should be considered along with the mother's clinical need for DAYBUE or DAYBUE STIX and any potential adverse effects on the breastfed infant from the treatment or from the underlying maternal condition.

8.4 Pediatric Use

The safety and effectiveness of DAYBUE and DAYBUE STIX for the treatment of Rett syndrome have been established in pediatric patients aged 2 years and older. The safety and effectiveness of DAYBUE for the treatment of Rett syndrome in pediatric patients 5 years of age and older was established in a randomized, double-blind, placebo-controlled, 12-week study (Study 1), which included 108 pediatric patients age 5 to less than 12 years of age and 47 pediatric patients age 12 to less than 17 years of age [see Adverse Reactions (6.1) and Clinical Studies (14)]. Use of DAYBUE or DAYBUE STIX in patients 2 to 4 years of age is supported by evidence from Study 1 and pharmacokinetic and safety data in 13 pediatric patients 2 to 4 years of age treated with DAYBUE for 12 weeks [see Dosage and Administration (2.1), Adverse Reactions (6.1), Clinical Pharmacology (12.3), and Clinical Studies (14)].

Safety and effectiveness in pediatric patients less than 2 years of age have not been established.

Juvenile Animal Data

Oral administration of trofinetide (0, 150, 300, or 1000 mg/kg twice daily; 0, 300, 600, or 2000 mg/kg/day) to rats from postnatal day (PND) 13-14 through 28 weeks of age resulted in no adverse effects on growth or neurobehavioral function. Plasma exposures at the highest dose tested were similar to those in pediatric patients at recommended doses.

Oral administration of trofinetide (0, 150, 300, or 1000 mg/kg twice daily; 0, 300, 600, or 2000 mg/kg/day) to juvenile rats for 10 weeks beginning on PND 13-14 resulted in no adverse effects on sexual maturation or reproductive function. Plasma exposures at the highest dose tested were similar to those in pediatric patients at recommended doses.

8.5 Geriatric Use

Clinical studies of DAYBUE did not include patients 65 years of age and older to determine whether or not they respond differently from younger patients. This drug is known to be substantially excreted by the kidney. Because elderly patients are more likely to have decreased renal function, it may be useful to monitor renal function.

8.6 Renal Impairment

Mild renal impairment is not expected to impact the exposure of trofinetide; therefore, dosage adjustment is not necessary. Dosage adjustment of DAYBUE or DAYBUE STIX is recommended in patients with moderate renal impairment (adult: eGFR 30 to 59 mL/min; pediatric: eGFR 30 to 59 mL/min/1.73 m^2) [see Dosage and Administration (2.6), Clinical Pharmacology (12.3)]. Administration of DAYBUE or DAYBUE STIX to patients with severe renal impairment (eGFR less than 30 mL/min for adults or less than 30 mL/min/1.73 m^2 for pediatrics) is not recommended.

11 DESCRIPTION

DAYBUE oral solution and DAYBUE STIX for oral solution contain the active moiety trofinetide. The chemical name of trofinetide is (2S)-2-{[(2S)-1-(2-aminoacetyl)-2-methylpyrrolidine-2-carbonyl]amino}pentanedioic acid (IUPAC). The molecular formula of trofinetide is C13H21N3O6 and its molecular weight is 315.33 g/mol. The chemical structure is shown below.

Trofinetide is a white to off-white solid and is freely soluble in water.

DAYBUE oral solution is pink to red in color and contains 1 g of trofinetide in each 5 mL of solution (200 mg/mL). The oral solution also contains FD&C Red No. 40, maltitol, methylparaben sodium, propylparaben sodium, purified water, strawberry flavor, and sucralose as inactive ingredients.

DAYBUE STIX for oral solution is a white, off-white to pinkish powder to be dissolved in a cold to room temperature water or water-based beverage before administration and contains 5,000 mg, 6,000 mg, or 8,000 mg of trofinetide in each packet. The for oral solution powder contains natural strawberry flavor and sucralose as inactive ingredients.

12 CLINICAL PHARMACOLOGY

12.1 Mechanism of Action

The mechanism by which trofinetide exerts therapeutic effects in patients with Rett syndrome is unknown.

12.2 Pharmacodynamics

Cardiac Electrophysiology

At the maximum recommended dose in healthy adult subjects, trofinetide does not prolong the QT interval to any clinically relevant extent.

12.3 Pharmacokinetics

DAYBUE STIX for oral solution demonstrated comparable bioavailability to DAYBUE oral solution in adult healthy subjects under fasted state.

Trofinetide exhibits linear kinetics with no time- or dose-dependent effect on pharmacokinetic parameters. Systemic exposure to trofinetide was dose-proportional across the studied dose range. Minimal to no accumulation was observed following multiple-dose administration.

Absorption

The time to maximum drug concentration (Tmax) is about 2 to 3 hours after administration. Based on the mass balance study, at least 84% of the administered dose was absorbed following oral administration of 12,000 mg trofinetide.

Effect of Food

Coadministration of trofinetide with a high-fat meal had no impact on the total exposure (AUC0-inf) of trofinetide and reduced the peak plasma concentration (Cmax) by approximately 20% [see Dosage and Administration (2.1)].

Distribution

Following oral administration, the apparent volume of distribution of trofinetide in adult healthy subjects was approximately 80 L. Trofinetide protein binding in human plasma is less than 6%.

Elimination

The effective elimination half-life of orally administered trofinetide in healthy subjects is about 1.5 hours.

Metabolism

Trofinetide is not significantly metabolized by CYP450 enzymes. Hepatic metabolism is not a significant route of trofinetide elimination.

Excretion

Trofinetide is primarily excreted unchanged (approximately 80% of the dose) in urine, with minor excretion in feces.

Specific Populations

Pediatric Patients

The drug exposure of trofinetide in pediatric patients ages 2 to 4 years of age is similar to children older than 4 years and adults when following the recommended dosage [see Dosage and Administration (2.1)].

Patients with Renal Impairment

Based on population PK analysis of clinical trials data, patients with mild renal impairment (eGFR 60 to 89 mL/min/1.73 m^2) showed no significant impact on the exposure of trofinetide compared to patients with normal renal function. Based on a renal impairment study in adult subjects, the effect of moderate renal impairment (eGFR 30 to 59 mL/min) increases the exposure (AUC0-inf) of trofinetide approximately 80% compared to patients with normal renal function administered the same dose [see Dosage and Administration (2.6)]. The effect of severe renal impairment on the exposure of trofinetide has not been investigated [see Use in Specific Populations (8.6)].

Patients with Hepatic Impairment

The pharmacokinetics in patients with hepatic impairment have not been studied. However, hepatic impairment is not expected to impact the exposure of trofinetide because hepatic metabolism is not a significant route of trofinetide elimination.

Drug Interaction Studies

Clinical Studies

CYP3A and/or P-gp Substrates:

Coadministration of trofinetide 12,000 mg twice daily with 4 mg of loperamide (a moderately sensitive CYP3A substrate and a P-gp substrate) increased the AUC of loperamide by 1.73-fold and the Cmax by 1.95-fold [see Drug Interactions (7.1)]. Administration of trofinetide 2 hours prior to loperamide increased the AUC of loperamide by 1.22-fold and the Cmax by 1.44-fold.

In Vitro

Trofinetide is not a substrate of CYP450 enzymes, uridine diphosphate glucuronosyltransferase (UGT), or major drug transporters.

Cytochrome P450 (CYP450) Enzymes:

Trofinetide inhibits CYP3A [see Drug Interactions (7.1)]. Trofinetide inhibits CYP1A2, 2B6, 2C8, 2C19, and 2D6, but is not expected to result in clinically significant drug interactions. Trofinetide does not inhibit CYP2C9.

UDP-Glucuronosyltransferase (UGT):

Trofinetide inhibits UGT enzymes, UGT1A9, 2B7, and 2B15.

Transporter Systems:

Trofinetide inhibits P-gp [see Drug Interactions (7.1)], BCRP, and BSEP. Trofinetide inhibits OAT1, OCT2, OATP1B1, OATP1B3, MATE1, and MATE2-K, but is not expected to result in clinically significant drug interactions. Trofinetide does not inhibit OAT3.

13 NONCLINICAL TOXICOLOGY

13.1 Carcinogenesis, Mutagenesis, Impairment of Fertility

Carcinogenesis

Studies to evaluate the carcinogenic potential of trofinetide have not been conducted.

Mutagenesis

Trofinetide was negative in in vitro (bacterial reverse mutation, chromosomal aberration in Chinese hamster ovary cells) and in vivo (mouse micronucleus) assays.

Impairment of Fertility

Oral administration of trofinetide (0, 150, 450, or 1000 mg/kg twice daily; 0, 300, 900, or 2000 mg/kg/day) to male and female rats prior to and throughout mating and continuing in females through gestation day 7 resulted in no adverse effects on fertility or reproductive function. Plasma exposures at the highest dose tested were less than that in humans at the maximum recommended human dose of 12,000 mg/dose (24,000 mg/day).

14 CLINICAL STUDIES

DAYBUE STIX

The effectiveness of DAYBUE STIX has been established from an adequate and well-controlled study of DAYBUE for the treatment of Rett syndrome and demonstration of similar pharmacokinetics between DAYBUE STIX for oral solution and DAYBUE oral solution [see Clinical Pharmacology (12.3)]. Presented below is a display of the efficacy results of the adequate and well-controlled study of DAYBUE in patients with Rett syndrome.

DAYBUE

The efficacy of DAYBUE for the treatment of Rett syndrome was established in a 12-week randomized, double-blind, placebo-controlled study in patients with Rett syndrome 5 to 20 years of age (Study 1; NCT04181723).

Patients (N=187) had a diagnosis of typical Rett syndrome according to the Rett Syndrome Diagnostic Criteria with a documented disease-causing mutation in the MECP2 gene. Patients were randomized to receive DAYBUE (N=93) or matching placebo (N=94) for 12 weeks. The DAYBUE dosage was based on patient weight to achieve similar exposure in all patients [see Dosage and Administration (2.1)].

The co-primary efficacy measures were change from baseline after 12 weeks of treatment in the total score of the Rett Syndrome Behaviour Questionnaire (RSBQ) and the Clinical Global Impression-Improvement (CGI-I) score. The RSBQ is a 45-item rating scale completed by the caregiver that assesses a range of symptoms of Rett syndrome (breathing, hand movements or stereotypies, repetitive behaviors, night-time behaviors, vocalizations, facial expressions, eye gaze, and mood). Each item is scored as 0 (not true), 1 (somewhat or sometimes true), or 2 (very true or often true), with a maximum possible score of 90 points. Lower scores reflect lesser severity in signs and symptoms of Rett syndrome. The CGI-I is rated by clinicians to assess whether a patient has improved or worsened on a 7-point scale (1=very much improved to 7=very much worse) in which a decrease in score indicates improvement.

Treatment with DAYBUE demonstrated a statistically significant difference in favor of DAYBUE as compared to placebo on the co-primary efficacy endpoints, the change from baseline in RSBQ total score, and the CGI-I score at week 12 (Table 6, Figure 1, and Figure 2).

Table 6 Summary of Study 1 Efficacy Results
 |  | Mean Baseline Score (SE) | Mean Week 12 Score (SE) | LS Mean Change from Baseline to Week 12 (SE) | DAYBUE-Placebo Treatment Difference, LS Mean (95% CI) [Difference in LS mean from the mixed-effect model for repeated measure analysis] | p-value
RSBQ | DAYBUE | 43.7 (1.21) | 39.9 (1.38) | -4.9 (0.94) | -3.2 (-5.7, -0.6) | 0.018
RSBQ | Placebo | 44.5 (1.26) | 42.8 (1.42) | -1.7 (0.90) | -3.2 (-5.7, -0.6) | 0.018
CGI-I | DAYBUE | -- | 3.5 (0.08) | -- | -0.3 (-0.5, -0.1) | 0.003
CGI-I | Placebo | -- | 3.8 (0.06) | -- | -0.3 (-0.5, -0.1) | 0.003
CI=confidence interval; LS mean=least-squares mean; SE=standard error

Figure 1 Change From Baseline in RSBQ Total Score in Study 1

Figure 2 Distribution of CGI-I Scores for Patients Completing Study 1

16 HOW SUPPLIED/STORAGE AND HANDLING

16.1 How Supplied

DAYBUE (trofinetide) 200 mg/mL oral solution is a pink to red, strawberry flavored solution supplied in a round high-density polyethylene (HDPE) multi-dose bottle with a child-resistant closure containing 450 mL of oral solution (NDC 63090-660-01).

DAYBUE STIX (trofinetide) for oral solution is a white, off-white to pinkish powder with a strawberry flavor supplied in multi-layer aluminum packets as follows:

 | Package Configuration and NDC Number
Strength | Individual Packet | Carton of 60 Packets
5,000 mg | 63090-663-01 | 63090-663-60
6,000 mg | 63090-664-01 | 63090-664-60
8,000 mg | 63090-665-01 | 63090-665-60

16.2 Storage and Handling

DAYBUE Oral Solution

Store DAYBUE in an upright position refrigerated at 2°C to 8°C (36°F to 46°F). Do not freeze.

Keep the child-resistant cap tightly closed.

Discard any unused DAYBUE oral solution after 14 days of first opening the bottle.

DAYBUE STIX for Oral Solution

Store DAYBUE STIX packets at 20°C to 25°C (68°F to 77°F); excursions permitted between 15°C and 30°C (59°F and 86°F) [see USP Controlled Room Temperature].

17 PATIENT COUNSELING INFORMATION

Advise the caregiver or patient to read the FDA-approved patient labeling (Patient Information).

Preparation and Administration

Advise the caregiver or patient that DAYBUE or DAYBUE STIX may be given orally or via gastrostomy (G) tube; doses administered via gastrojejunal (GJ) tubes must be administered through the G-port. DAYBUE or DAYBUE STIX may be taken with or without food [see Dosage and Administration (2.1)].

Instruct the caregiver or patient to obtain a calibrated measuring device, such as an oral syringe or oral dosing cup, from the pharmacy. A household measuring cup, teaspoon, or tablespoon is not an adequate measuring device [see Dosage and Administration (2.2, 2.3)].

DAYBUE Oral Solution

Instruct the caregiver or patient to discard any unused DAYBUE oral solution after 14 days from first opening the bottle.

DAYBUE STIX for Oral Solution

Advise the caregiver or patient that DAYBUE STIX for oral solution powder must be dissolved in a cold to room temperature water or water-based beverage (juice, tea, lemonade, limeade, or liquid hydration) prior to administration [see Dosage and Administration (2.3)]. Instruct the caregiver or patient on how much water or water-based beverage is needed to dissolve the contents of DAYBUE STIX packet(s).

Instruct the caregiver or patient to administer the prepared oral solution immediately and not to store for future use. Any prepared oral solution not administered must be discarded.

Instruct patients to not attempt to use partial packets to prepare a dose.

Diarrhea

Advise the caregiver or patient that DAYBUE or DAYBUE STIX can cause diarrhea. Instruct the patient to stop taking laxatives before starting DAYBUE or DAYBUE STIX. If diarrhea occurs, patients should notify their healthcare provider, consider starting antidiarrheal treatment, and monitor hydration status and increase oral fluids, if needed [see Warnings and Precautions (5.1)].

Weight Loss

Inform the caregiver or patient that DAYBUE or DAYBUE STIX may cause weight loss and to notify their healthcare provider if weight loss occurs [see Warnings and Precautions (5.2)].

Vomiting

Advise the caregiver or patient that DAYBUE or DAYBUE STIX can cause vomiting and if vomiting occurs after DAYBUE or DAYBUE STIX administration, do not take an additional dose, but continue with the next scheduled dose [see Dosage and Administration (2.5)]. Instruct patients to notify their healthcare provider if vomiting does not stop despite medical management [see Warnings and Precautions (5.3)].

Storage

DAYBUE Oral Solution

Keep bottles of DAYBUE upright and refrigerated before and after opening. Do not freeze [see How Supplied/Storage and Handling (16.2)].

Marketed by:
Acadia Pharmaceuticals Inc. San Diego, CA 92130 USA

DAYBUE is a registered trademark of Acadia Pharmaceuticals Inc.
©2025 Acadia Pharmaceuticals Inc. All rights reserved.

PATIENT INFORMATION

DAYBUE® (day-BYOO)
(trofinetide)
oral solution

DAYBUE® STIX (day-BYOO STIX)
(trofinetide)
for oral solution

What is DAYBUE or DAYBUE STIX?

- DAYBUE or DAYBUE STIX are prescription medicines used to treat Rett syndrome in adults and children 2 years of age and older.

It is not known if DAYBUE or DAYBUE STIX is safe and effective in children under 2 years of age.

Before taking DAYBUE or DAYBUE STIX, tell your healthcare provider about all of your medical conditions, including if you:

- have kidney problems.
- are pregnant or plan to become pregnant. It is not known if DAYBUE or DAYBUE STIX will harm your unborn baby.
- are breastfeeding or plan to breastfeed. It is not known if DAYBUE or DAYBUE STIX passes into your breast milk. Talk to your healthcare provider about the best way to feed your baby while taking DAYBUE or DAYBUE STIX.

Tell your healthcare provider about all of the medicines you take, including prescription and over-the-counter medicines, vitamins, and herbal supplements.
Taking DAYBUE or DAYBUE STIX with certain medicines may affect the way other medicines work and can cause serious side effects.
Know the medicines you take. Keep a list of them to show your healthcare provider and pharmacist when you get a new medicine.

How should I take DAYBUE or DAYBUE STIX?

- Take DAYBUE or DAYBUE STIX exactly as your healthcare provider tells you to take it.
- If you have kidney problems, talk to your healthcare provider about the right dose of DAYBUE or DAYBUE STIX.
- If you take laxatives, stop taking them before starting treatment with DAYBUE or DAYBUE STIX.
- DAYBUE or DAYBUE STIX may be given by mouth or through a gastrostomy (G) tube. If DAYBUE or DAYBUE STIX is given through a gastrojejunal (GJ) tube, the G-port must be used.
- DAYBUE or DAYBUE STIX may be taken with or without food.
- Your pharmacist should provide an oral syringe or dosing cup that is needed to measure your prescribed dose of DAYBUE or the amount of liquid to mix with DAYBUE STIX powder. A household measuring cup, teaspoon, or tablespoon is not an adequate measuring device.
- If you are taking DAYBUE oral solution:
  - Throw away any unused DAYBUE oral solution after 14 days of first opening the bottle.
- If you are taking DAYBUE STIX for oral solution:
  - Open each packet only when you are ready to use it.
  - DAYBUE STIX powder must be dissolved in cold to room temperature water or water-based beverage (juice, tea, lemonade, or liquid hydration).
  - Your healthcare provider will tell you how much cold to room temperature water or water-based beverage to use to dissolve the powder in each packet.
  - Empty the entire contents of the DAYBUE STIX packets needed for your prescribed dose into the measured liquid. Do not attempt to use part of a packet.
  - Stir until the powder is completely dissolved.
  - After the powder is dissolved, take the prepared oral solution right away. Do not store for future use.
  - Throw away any prepared oral solution that was not taken.
- Your healthcare provider may change your dose or stop treatment with DAYBUE or DAYBUE STIX if needed.
- If you vomit after taking a dose of DAYBUE or DAYBUE STIX, do not take another dose to make up for that dose. Wait and take the next dose at your usual time. Call your healthcare provider if your vomiting does not stop.
- If you miss a dose of DAYBUE or DAYBUE STIX, skip that dose and take your next dose at your usual time. Do not take 2 doses to make up the missed dose.

What are the possible side effects of DAYBUE or DAYBUE STIX?
DAYBUE or DAYBUE STIX may cause side effects, including:

- Diarrhea. Diarrhea is a common side effect of DAYBUE or DAYBUE STIX that can sometimes be severe. Diarrhea may cause you to lose too much water from your body (dehydration). Tell your healthcare provider if you have diarrhea while taking DAYBUE or DAYBUE STIX. Your healthcare provider may ask you to increase the amount you drink or take antidiarrheal medicine as needed.
- Weight loss. DAYBUE or DAYBUE STIX can cause weight loss. Tell your healthcare provider if you notice you are losing weight at any time during treatment with DAYBUE or DAYBUE STIX.
- Vomiting. Vomiting is a common side effect of DAYBUE or DAYBUE STIX. Sometimes vomit can get into your lungs (aspiration), which could cause an infection (aspiration pneumonia). Tell your healthcare provider if you have severe vomiting or if vomiting happens often.

The most common side effects of DAYBUE or DAYBUE STIX include diarrhea and vomiting.
These are not all the possible side effects of DAYBUE or DAYBUE STIX. Tell your healthcare provider if you have any side effects that bother you or do not go away. For more information, ask your healthcare provider or pharmacist. Call your doctor for medical advice about side effects. You may report side effects to FDA at 1-800-FDA-1088.

How should I store DAYBUE or DAYBUE STIX?

- DAYBUE oral solution:
  - Store DAYBUE oral solution bottle in the refrigerator between 36°F to 46°F (2°C to 8°C). Do not freeze.
  - Keep DAYBUE oral solution bottle in an upright position.
  - Keep the child-resistant cap on the bottle tightly closed.
- DAYBUE STIX for oral solution:
  - Store DAYBUE STIX for oral solution powder packets at room temperature between 68°F to 77°F (20°C to 25°C).

Keep DAYBUE, DAYBUE STIX, and all medicines out of the reach of children.

General information about the safe and effective use of DAYBUE or DAYBUE STIX.
Medicines are sometimes prescribed for purposes other than those listed in a Patient Information leaflet. Do not use DAYBUE or DAYBUE STIX for a condition for which it was not prescribed. Do not give DAYBUE or DAYBUE STIX to other people, even if they have the same symptoms that you have. It may harm them. You can ask your pharmacist or healthcare provider for information about DAYBUE or DAYBUE STIX that is written for health professionals.

What are the ingredients in DAYBUE or DAYBUE STIX?
Active ingredient: trofinetide
DAYBUE oral solution inactive ingredients: FD&C Red No. 40, maltitol, methylparaben sodium, propylparaben sodium, purified water, strawberry flavor, and sucralose.
DAYBUE STIX for oral solution inactive ingredients: natural strawberry flavor and sucralose.
Marketed by Acadia Pharmaceuticals Inc., San Diego, CA 92130 USA
DAYBUE is a registered trademark of Acadia Pharmaceuticals Inc.
©2025 Acadia Pharmaceuticals Inc. All rights reserved.
For more information, go to www.daybue.com or call 1-844-422-2342.

This Patient Information has been approved by the U.S. Food and Drug Administration

Issued: 12/2025

PRINCIPAL DISPLAY PANEL – 450 ML ORAL SOLUTION BOTTLE LABEL

NDC 63090-660-01

450 mL
Rx only

Daybue™
(trofinetide)
oral solution

200 mg/mL

Recommended Dosage:
See prescribing information.

For oral or G-tube administration only.

PRINCIPAL DISPLAY PANEL – 450 ML ORAL SOLUTION BOTTLE CARTON

NDC 63090-660-01

Daybue™
(trofinetide)
oral solution

200 mg/mL

Recommended Dosage:
See prescribing information.

For oral or G-tube administration only.

450 mL

Rx only

PRINCIPAL DISPLAY PANEL – 5,000 MG FOR ORAL SOLUTION POWDER PACKET

NDC 63090-663-01

Daybue® Stix
(trofinetide)
for oral solution

5,000 mg

For Oral or G-tube administration only

Keep out of reach of children

Rx Only

PRINCIPAL DISPLAY PANEL – 5,000 MG FOR ORAL SOLUTION POWDER CARTON

NDC 63090-663-60

Daybue® Stix
(trofinetide)
for oral solution

5,000 mg
per packet

For Oral or G-tube
administration only

60 Packets

Rx Only

PRINCIPAL DISPLAY PANEL – 6,000 MG FOR ORAL SOLUTION POWDER PACKET

NDC 63090-664-01

Daybue® Stix
(trofinetide)
for oral solution

6,000 mg

For Oral or G-tube administration only

Keep out of reach of children

Rx Only

PRINCIPAL DISPLAY PANEL – 6,000 MG FOR ORAL SOLUTION POWDER CARTON

NDC 63090-664-60

Daybue® Stix
(trofinetide)
for oral solution

6,000 mg
per packet

For Oral or G-tube
administration only

60 Packets

Rx Only

PRINCIPAL DISPLAY PANEL – 8,000 MG FOR ORAL SOLUTION POWDER PACKET

NDC 63090-665-01

Daybue® Stix
(trofinetide)
for oral solution

8,000 mg

For Oral or G-tube administration only

Keep out of reach of children

Rx Only

PRINCIPAL DISPLAY PANEL – 8,000 MG FOR ORAL SOLUTION POWDER CARTON

NDC 63090-665-60

Daybue® Stix
(trofinetide)
for oral solution

8,000 mg
per packet

For Oral or G-tube
administration only

60 Packets

Rx Only